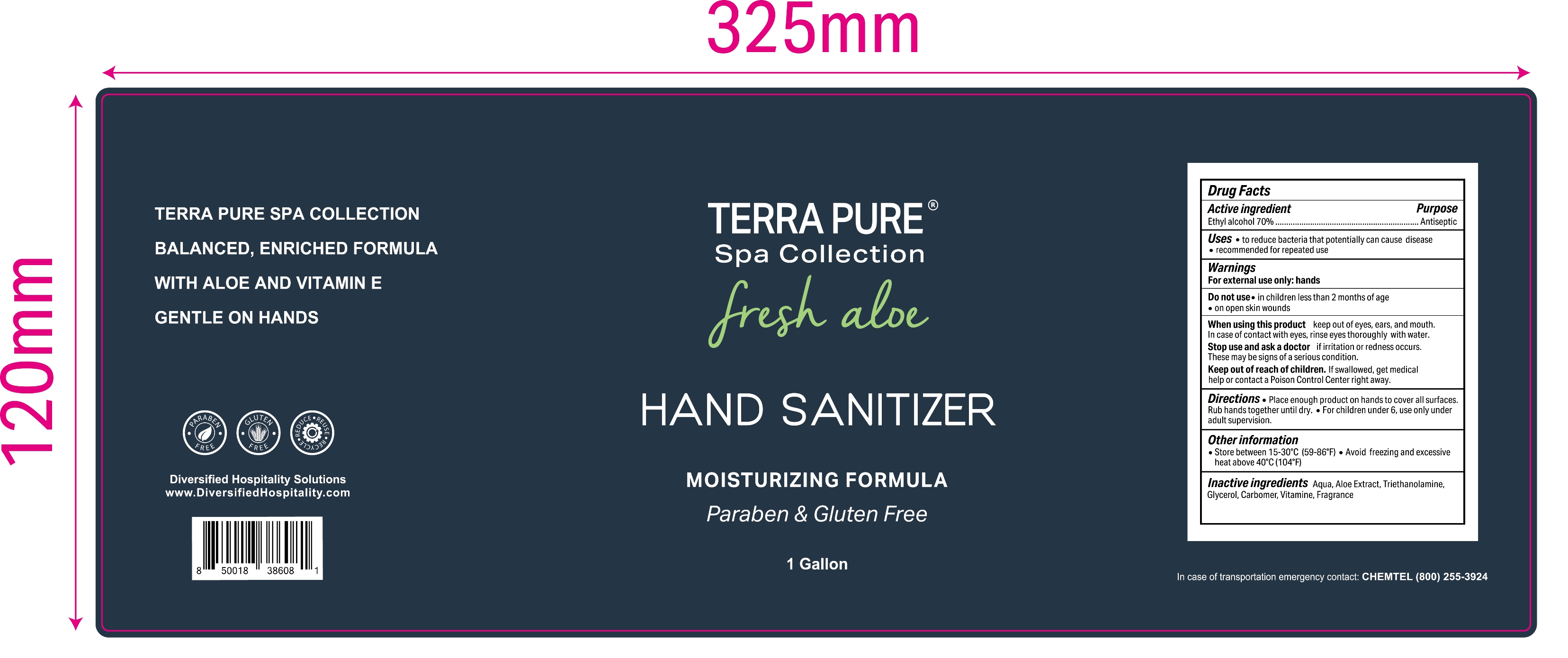 DRUG LABEL: TERRA PURE Spa Collection Fresh Aloe Hand Sanitizer Paraben and Gluten Free
NDC: 77573-003 | Form: SOLUTION
Manufacturer: Jiangsu Aimeili Cosmetic Co.,Ltd.
Category: otc | Type: HUMAN OTC DRUG LABEL
Date: 20240105

ACTIVE INGREDIENTS: ALCOHOL 70 mL/100 mL
INACTIVE INGREDIENTS: TROLAMINE; WATER; CARBOMER 940; GLYCEROL FORMAL; ALOE; .ALPHA.-TOCOPHEROL ACETATE

77573-003

Active Ingredient

Ethyl Alcohol 70% v/v

Purpose

Antiseptic

Use

To reduce bacteria that potentially can cause disease

Recommended for repeated use

Warnings

For external use only -hands

Flammable. Keep away from heat and flame

When using this product keep out of eyes, ears, and mouth. In case of contact with eyes, rinse eyes thoroughly with water.

Do not use

In children less than 2 months of age

On open sin wounds

Stop use and ask a doctor if irritation or redness occurs. These may be signs of a serious condition

Keep out of reach of children. If swallowed, get medical help or contact a Poison Control Center right away.

Directions

- Place enough product on hands to cover all surfaces. Rub hands together until dry.
- For children under 6, use only under adult supervision

Other information

Store between 15-30C (59 to 86F)

Avoid freezing and excessive heat above 40C (104F)

Inactive ingredients

Water, aloe extract, triethanolamine, glycerol, carbomer, vitamin E, Fragrance